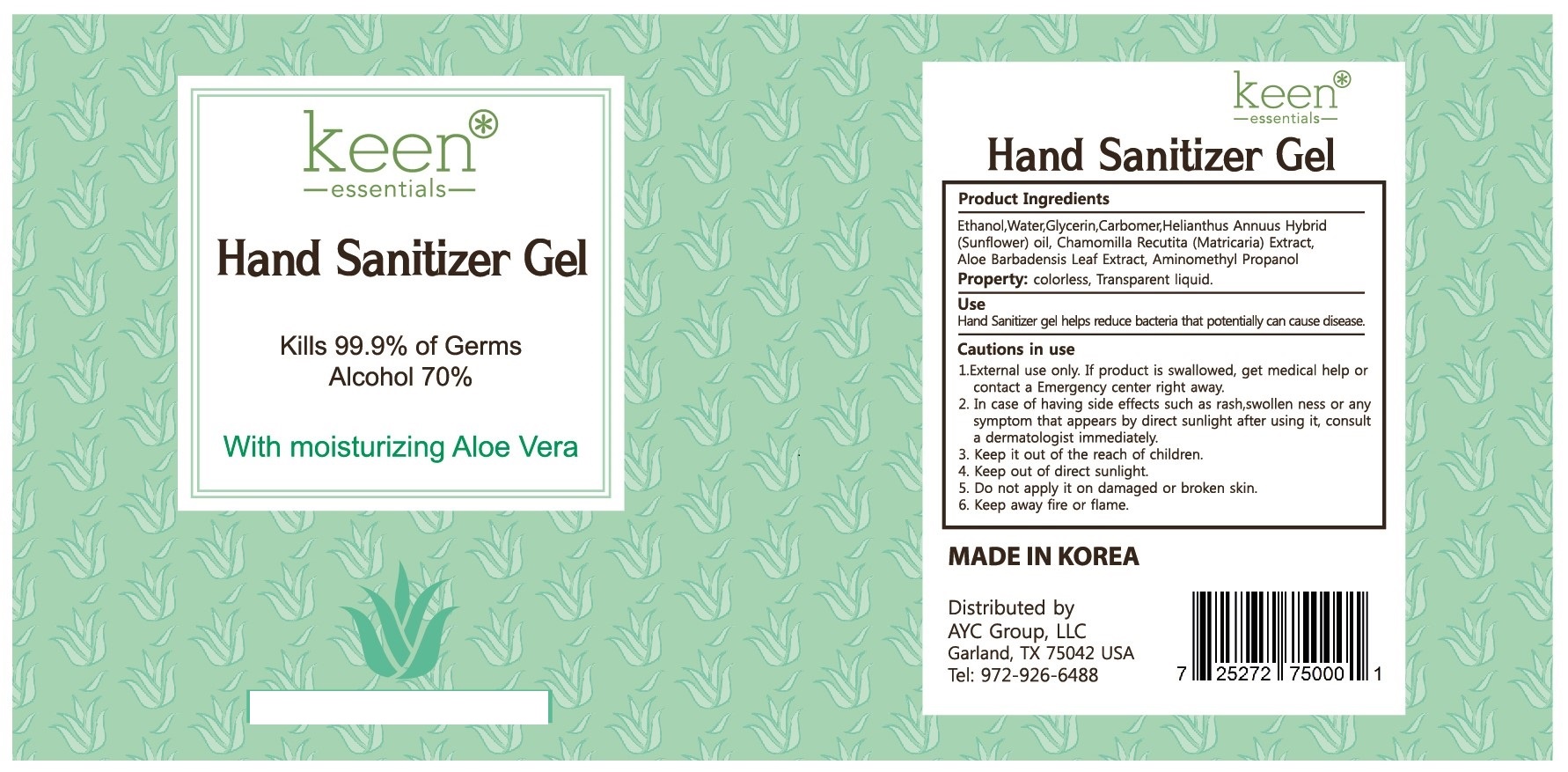 DRUG LABEL: KEEN ESSENTIALS HAND SANITIZER
NDC: 78924-0001 | Form: GEL
Manufacturer: YESROAD COSMETICS CO.,LTD
Category: otc | Type: HUMAN OTC DRUG LABEL
Date: 20200828

ACTIVE INGREDIENTS: ALCOHOL 70 mL/100 mL
INACTIVE INGREDIENTS: 1,2-HEXANEDIOL; AMINOMETHYLPROPANOL; MATRICARIA RECUTITA; SUNFLOWER OIL; BUTYLENE GLYCOL; GLYCERIN; WATER; CARBOMER 940; ALOE VERA LEAF

ACTIVE INGREDIENT

alcohol

INACTIVE INGREDIENT

Water
Glycerin

Carbomer

Helianthus Annuus Hybrid (Sunflower) oil
Chamomilla Recutita (Matricaria) Extract
Butylene Glycol

Aloe Barbadensis Leaf Extract

Butylene Glycol

1,2-Hexanediol

Aminomethyl Propanol

PURPOSE

for hand-washing to decrease bacteria on the skin, only when water is not available

Keep out of reach of children

INDICATIONS AND USAGE

wet hands thoroughly with product and allow to dry without wiping

WARNINGS

Flammable, keep away from fire and flames
Fot external use only.

DOSAGE AND ADMINISTRATION

For external use only